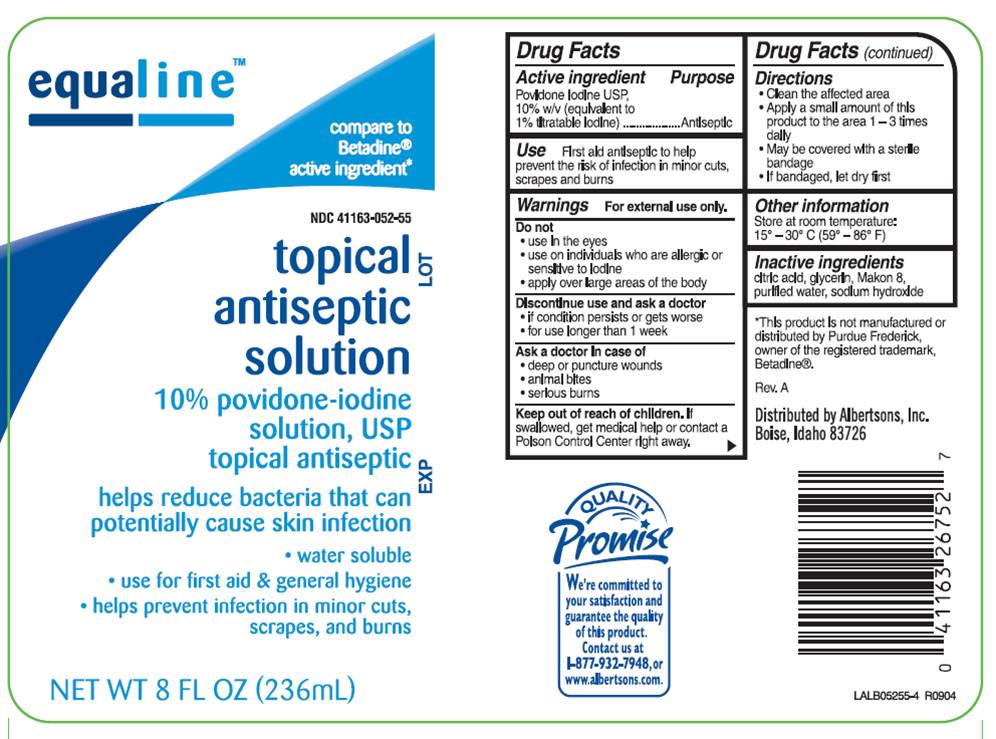 DRUG LABEL: Povidone Iodine
NDC: 41163-052 | Form: SOLUTION
Manufacturer: Supervalu Inc
Category: otc | Type: HUMAN OTC DRUG LABEL
Date: 20100202

ACTIVE INGREDIENTS: povidone-iodine 0.10 mg/1 mL
INACTIVE INGREDIENTS: citric acid monohydrate; glycerin; sodium hydroxide; water

DRUG FACTS

ACTIVE INGREDIENT

Povidone Iodine,10% w/v (equivalent to 1% titratable iodine)

PURPOSE

Antiseptic

USE

First aid antiseptic to help prevent the risk of infection in minor cuts, scrapes and burns

WARNINGS

For external use only.

Do not

- use in the eyes
- use on individuals who are allergic or sensitive to iodine
- apply over large areas of the body

Discontinue use and ask a doctor

- if condition persists or gets worse
- for use longer than 1 week

Ask a doctor in case of

- deep or puncture wounds
- animal bites
- serious burns

Keep out of reach of children

If swallowed, get medical help or contact a Poison Control Center right away.

DIRECTIONS

- Clean the affected area
- Apply a small amount of this product to the area 1-3 times daily
- May be covered with a sterile bandage
- If bandaged, let dry first

OTHER INFORMATION

Store at room temperature 15° - 30° C (59° - 86° F)

INACTIVE INGREDIENTS

citric acid, glycerin, Makon 8, purified water, sodium hydroxide

LABEL INFORMATION

EQUALINE

*Compare to Betadine active ingredient®

NDC 24385-053-55

Topical Antiseptic Solution

10% povidone-iodine solution, USP
topical antiseptic

helps reduce bacteria that can potentially cause skin infection

- water soluble
- use for first aid and general hygiene
- helps prevent infection in minor cuts, scrapes and burns

NET WT 8 FL OZ (236 mL)
*This product is not manufactured of distributed by Purdue Frederick, owner of the registered trademark, Betadine®.

Distributed by Albertsons, Inc.
Boise, Idaho 83726

We're committed to your satisfaction and guarantee the quality of this product. Contact us at 1-877-932-7948 or www.albertsons.com.